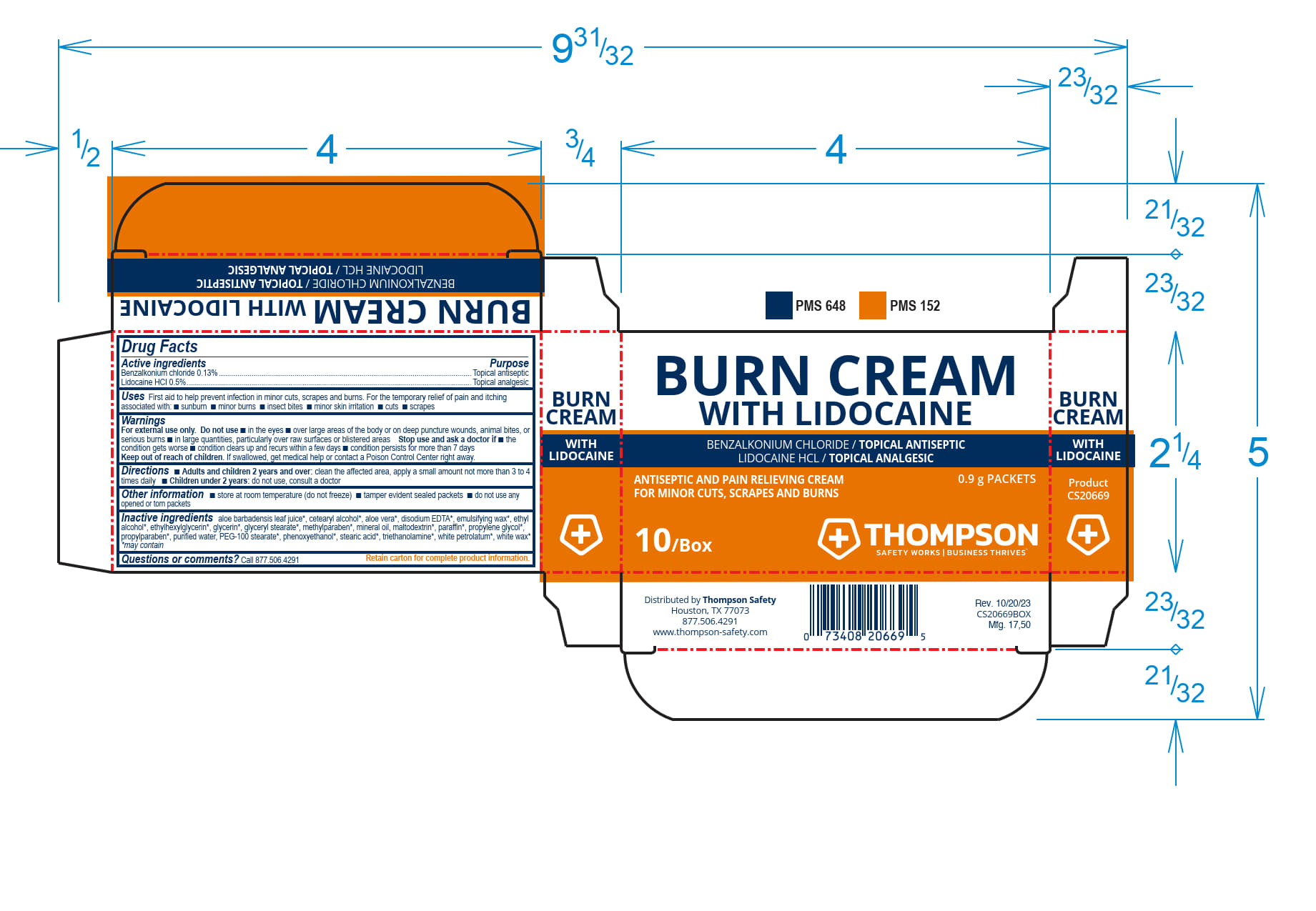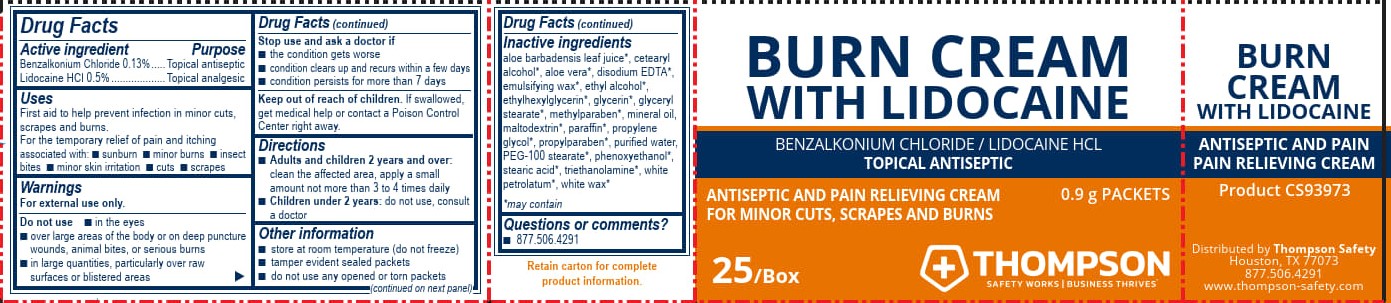 DRUG LABEL: Thompson Burn Cream with Lidocain
NDC: 73408-060 | Form: CREAM
Manufacturer: Thompson Safety
Category: otc | Type: HUMAN OTC DRUG LABEL
Date: 20250908

ACTIVE INGREDIENTS: BENZALKONIUM CHLORIDE 1.3 mg/1 g; LIDOCAINE HYDROCHLORIDE 5 mg/1 g
INACTIVE INGREDIENTS: PROPYLENE GLYCOL; CETEARYL ALCOHOL; WATER; TRIETHANOLAMINE; EDETATE DISODIUM; PEG-100 STEARATE; GLYCERIN; PHENOXYETHANOL; MALTODEXTRIN; ALOE VERA LEAF; GLYCERYL STEARATE SE; MINERAL OIL; ETHYLHEXYLGLYCERIN

Thompson Safety Burn Cream with Lidocaine

Drug Facts

Active Ingredients

Benzalkonium Chloride 0.13%

Lidocaine HCI 0.5%

Purpose

Topical antiseptic

Topical analgesic

Uses

First aid to help prevent infection in minor cuts, scrapes and burns.

For the temporary relief of pain and itching associated with:

- sunburn
- minor burns
- insect bites
- minor skin irritaion
- cuts
- scrapes

Warnings

For external use only.

Do not use

- in the eyes
- over large areas of the body or on deep puncture wounds, animal bites, or serious burns
- in large quantities, particularly over raw surfaces or blistered areas

Stop use and ask a doctor if

- the condition gets worse
- condition clears up and recurs within a few days
- condition persists for more than 7 days

Keep out of reach of children.

If swaallowed, get medical help or contact a Poison Control Center right away.

Directions

- Adults and childred 2 years and over:

clean the affected area, apply a small amount not more than 3 to 4 times daily

- Children under 2 years:

do not use, consult a doctor

Other Information

- store at room temperature (do not freeze)
- tamper evident sealed packets
- do not use any opened or torn packets

Inactive ingredients

aloe barbadensis leaf juice*, cetearyl alcohol*, aloe vera*, disodium EDTA*, emulsifying wax*, ethyl alcohol*, ethylhexlglycerin*, glycerin*, glyceryl stearate*, methylparaben*, mineral oil, maltodextrin*, paraffin*, propylene glycol*, propylparaben*, purifed water*, PEG-100 stearate*, phenoxyethanol*, stearic acid*, triethanolamine*, white petrolatum*, white wa*x

*may contain

Questions or comments?

- 877.506.4291

PACKAGE LABEL

BURN CREAM

WITH LIDOCAINE

BENZALKONIUM CHLROIDE / LIDOCAINE HCL

TOPICAL ANTISEPTIC

ANTISEPTIC AND PAIN RELIEVING CREAM 0.9 g PACKETS

FOR MINOR CUTS, SCRAPES AND BURNS

25 / BOX THOMPSON

SAFETY WORKS BUSINESS THRIVES